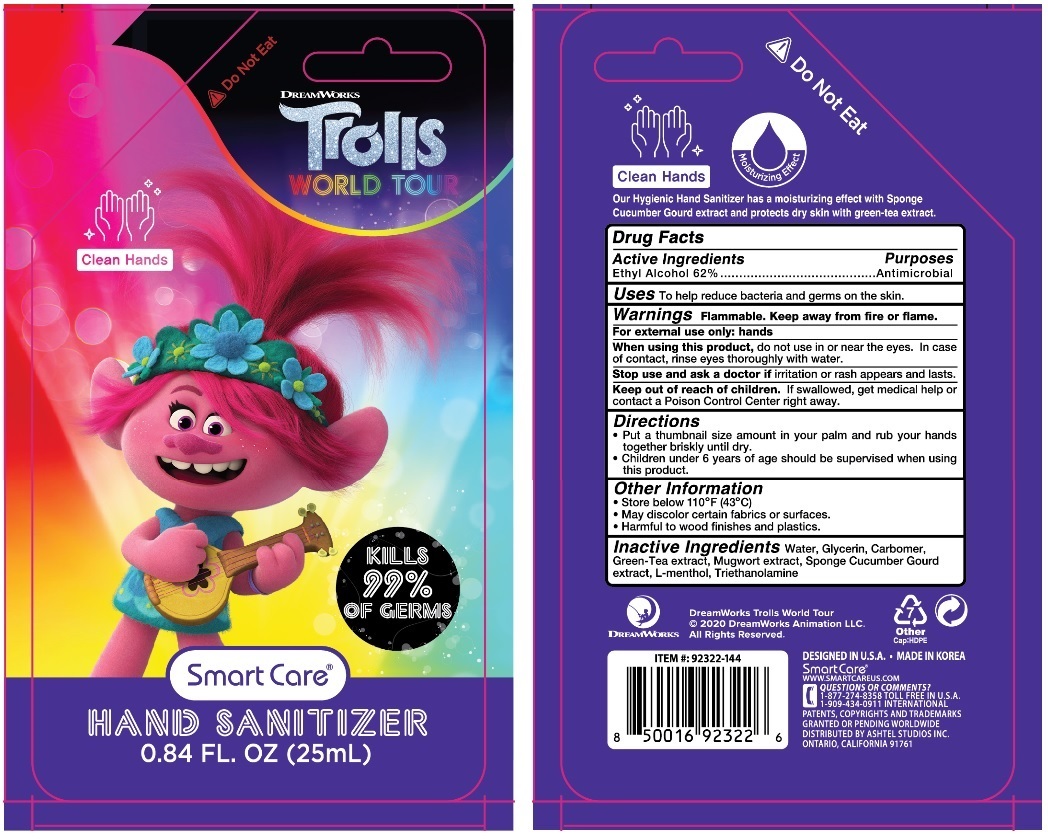 DRUG LABEL: Trolls Hand Sanitizer 0.84 oz
NDC: 70108-047 | Form: GEL
Manufacturer: Ashtel Studios, Inc
Category: otc | Type: HUMAN OTC DRUG LABEL
Date: 20200420

ACTIVE INGREDIENTS: ALCOHOL 62 mL/100 mL
INACTIVE INGREDIENTS: WATER; GLYCERIN; CARBOMER HOMOPOLYMER, UNSPECIFIED TYPE; GREEN TEA LEAF; ARTEMISIA PRINCEPS LEAF; LUFFA AEGYPTIACA FRUIT; LEVOMENTHOL; TROLAMINE

Smart Care® HAND SANITIZER

Active Ingredients

Ethyl Alcohol 62%

Purposes

Antimicrobial

Uses

To help reduce bacteria and germs on the skin.

Warnings

Flammable, keep away from fire or flame.

For external use only: hands

When using this product, do not use in or near the eyes. In case of contact, rinse eyes thoroughly with water.

Stop use and ask a doctor if irritation or rash appears and lasts.

Keep out of reach of children

If swallowed get medical help or contact a Poison Control Center right away.

Directions

• Put a thumbnail size amount in your palm and rub your hands together briskly until dry.

• Children under 6 years of age should be supervised when using this product.

Other Information

• Store below 110°F (43°C).

• May discolor certain fabrics or surfaces.

• Harmful to wood finishes and plastics.

Inactive Ingredients

Water, Glycerin, Carbomer, Green-Tea extract, Mugwort extract, Sponge Cucumber Gourd extract, L-menthol, Triethanolamine

DREAMWORKS

TROLLS WORLD TOUR

Clean Hands

KILLS 99% OF GERMS

Do Not Eat

Moisturizing Effect

Our Hygienic Hand Sanitizer has a moisturizing effect with Sponge Cucumber Gourd extract and protects dry skin with green-tea extract.

© 2020 DreamWorks Animation LLC.

All Rights Reserved.

DESIGNED IN U.S.A. • MADE IN KOREA

WWW.SMARTCAREUS.COM

QUESTIONS OR COMMENTS?

1-877-274-8358 TOLL FREE IN U.S.A.

1-909-434-0911 INTERNATIONAL

PATENTS, COPYRIGHTS AND TRADEMARKS GRANTED OR PENDING WORLDWIDE

DISTRIBUTED BY ASHTEL STUDIOS INC. ONTARIO, CALIFORNIA 91761